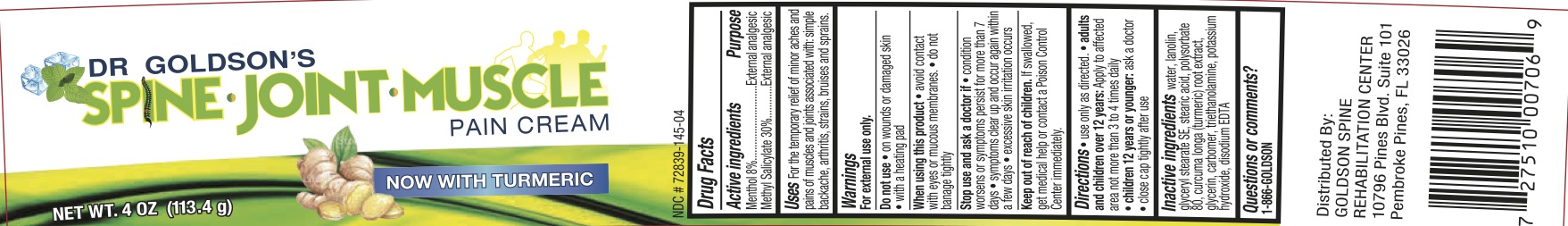 DRUG LABEL: Dr Goldsons Pain
NDC: 72839-145 | Form: CREAM
Manufacturer: Derma Care Research Labs, LLC
Category: otc | Type: HUMAN OTC DRUG LABEL
Date: 20241219

ACTIVE INGREDIENTS: METHYL SALICYLATE 30 g/100 g; MENTHOL 8 g/100 g
INACTIVE INGREDIENTS: CARBOMER 940; TROLAMINE; WATER; STEARIC ACID; GLYCERIN; LANOLIN; GLYCERYL STEARATE SE; POLYSORBATE 80; TURMERIC; EDETATE DISODIUM; POTASSIUM HYDROXIDE

Dr Goldsons Pain Relief Cream

ACTIVE INGREDIENT

Menthol 8%, Methyl Salicylate 30%

PURPOSE

External Analgesic

INDICATIONS AND USAGE

For the temporary relief of minor aches and pains of muscles and joints associated with simple backache, arthritis, strains, bruises, and sprains.

WARNINGS

For external use only. Do not use on wounds or damaged skin or with a heating pad. When using this product avoid contact with eyes or mucous membranes, do not bandage tightly. Stop use and ask a doctor if condition worsens, if symptoms persist for more than 7 days or clear up and occur again within a few days, excessive skin irritation occurs.

KEEP OUT OF REACH OF CHILDREN

If swallowed, get medical help or contact a Poison Control Center right away.

DOSAGE AND ADMINISTRATION

Use only as directed. Adults and children over 12 years: apply to affected area not more than 3 to 4 times daily. Children 12 years oryounger: ask a doctor. Close cap tightly after use.

INACTIVE INGREDIENT

Water, lanolin, glyceryl stearate SE, stearic acid, polysorbate 80, curcuma longa (turmeric) root extract, glycerin, carbomer, triethanolamine, potassium hydroxide, disodium EDTA